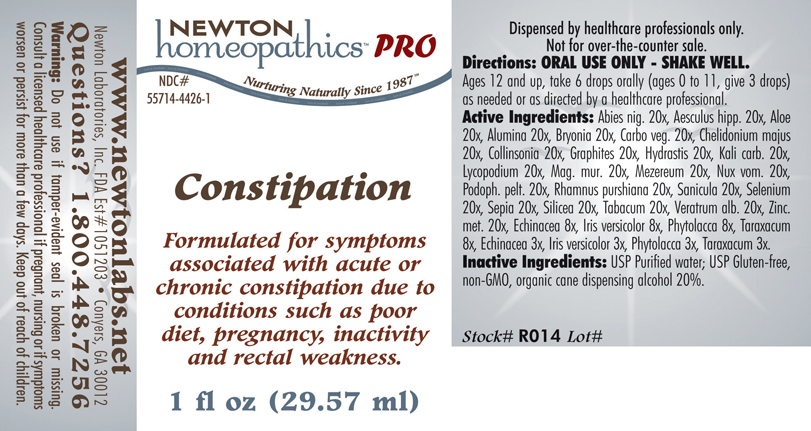 DRUG LABEL: Constipation 
NDC: 55714-4426 | Form: LIQUID
Manufacturer: Newton Laboratories, Inc.
Category: homeopathic | Type: HUMAN PRESCRIPTION DRUG LABEL
Date: 20110601

ACTIVE INGREDIENTS: Picea Mariana Resin 20 [hp_X]/1 mL; Horse Chestnut 20 [hp_X]/1 mL; Aloe 20 [hp_X]/1 mL; Aluminum Oxide 20 [hp_X]/1 mL; Bryonia Alba Root 20 [hp_X]/1 mL; Activated Charcoal 20 [hp_X]/1 mL; Chelidonium Majus 20 [hp_X]/1 mL; Collinsonia Canadensis Root 20 [hp_X]/1 mL; Graphite 20 [hp_X]/1 mL; Goldenseal 20 [hp_X]/1 mL; Potassium Carbonate 20 [hp_X]/1 mL; Lycopodium Clavatum Spore 20 [hp_X]/1 mL; Magnesium Chloride 20 [hp_X]/1 mL; Daphne Mezereum Bark 20 [hp_X]/1 mL; Strychnos Nux-vomica Seed 20 [hp_X]/1 mL; Podophyllum 20 [hp_X]/1 mL; Frangula Purshiana Bark 20 [hp_X]/1 mL; Sanicula Europaea Whole 20 [hp_X]/1 mL; Selenium 20 [hp_X]/1 mL; Sepia Officinalis Juice 20 [hp_X]/1 mL; Silicon Dioxide 20 [hp_X]/1 mL; Tobacco Leaf 20 [hp_X]/1 mL; Veratrum Album Root 20 [hp_X]/1 mL; Zinc 20 [hp_X]/1 mL; Echinacea, Unspecified 8 [hp_X]/1 mL; Iris Versicolor Root 8 [hp_X]/1 mL; Phytolacca Americana Root 8 [hp_X]/1 mL; Taraxacum Officinale 8 [hp_X]/1 mL; Echinacea, Unspecified 3 [hp_X]/1 mL; Iris Versicolor Root 3 [hp_X]/1 mL; Phytolacca Americana Root 3 [hp_X]/1 mL; Taraxacum Officinale 3 [hp_X]/1 mL
INACTIVE INGREDIENTS: Alcohol

Constipation

PRODUCT NAME & INDICATIONS SECTION

Constipation Formulated for symptoms associated with acute or chronic constipation due to conditions such as poor diet, pregnancy, inactivity and rectal weakness.

DIRECTION SECTION

Directions: ORAL USE ONLY - SHAKE WELL. Ages 12 and up, take 6 drops orally (ages 0 to 11, give 3 drops) as needed or as directed by a healthcare professional.

ACTIVE INGREDIENT SECTION

Abies nig. 20x, Aesculus hipp. 20x, Aloe 20x, Alumina 20x, Bryonia 20x, Carbo veg. 20x, Chelidonium majus 20x, Collinsonia 20x, Graphites 20x, Hydrastis 20x, Kali carb. 20x, Lycopodium 20x, Mag. mur. 20x, Mezereum 20x, Nux vom. 20x, Podoph. pelt. 20x, Rhamnus purshiana 20x, Sanicula 20x, Selenium 20x, Sepia 20x, Silicea 20x, Tabacum 20x, Veratrum alb. 20x, Zinc.met. 20x, Echinacea 8x, Iris versicolor 8x, Phytolacca 8x, Taraxacum 8x, Echinacea 3x, Iris versicolor 3x, Phytolacca 3x, Taraxacum 3x.

PURPOSE SECTION

Formulated for symptoms associated with acute or chronic constipation due to conditions such as poor diet, pregnancy, inactivity and rectal weakness.

INACTIVE INGREDIENT SECTION

Inactive Ingredients: USP Purified Water; USP Gluten-free, non-GMO, organic cane dispensing alcohol 20%

QUESTIONS? SECTION

www.newtonlabs.net Newton Laboratories, Inc. FDA Est # 1051203 - Conyers, GA 30012
Questions? 1.800.448.7256

WARNINGS SECTION

Warning: Do not use if tamper - evident seal is broken or missing. Consult a licensed healthcare professional if pregnant, nursing or if symptoms worsen or persist for more than a few days. Keep out of reach of children.

OTC - PREGNANCY OR BREAST FEEDING SECTION

Consult a licensed healthcare professional if pregnant, nursing or if symptoms worsen or persist for more than a few days.

OTC - KEEP OUT OF REACH OF CHILDREN SECTION

Keep out of reach of children.